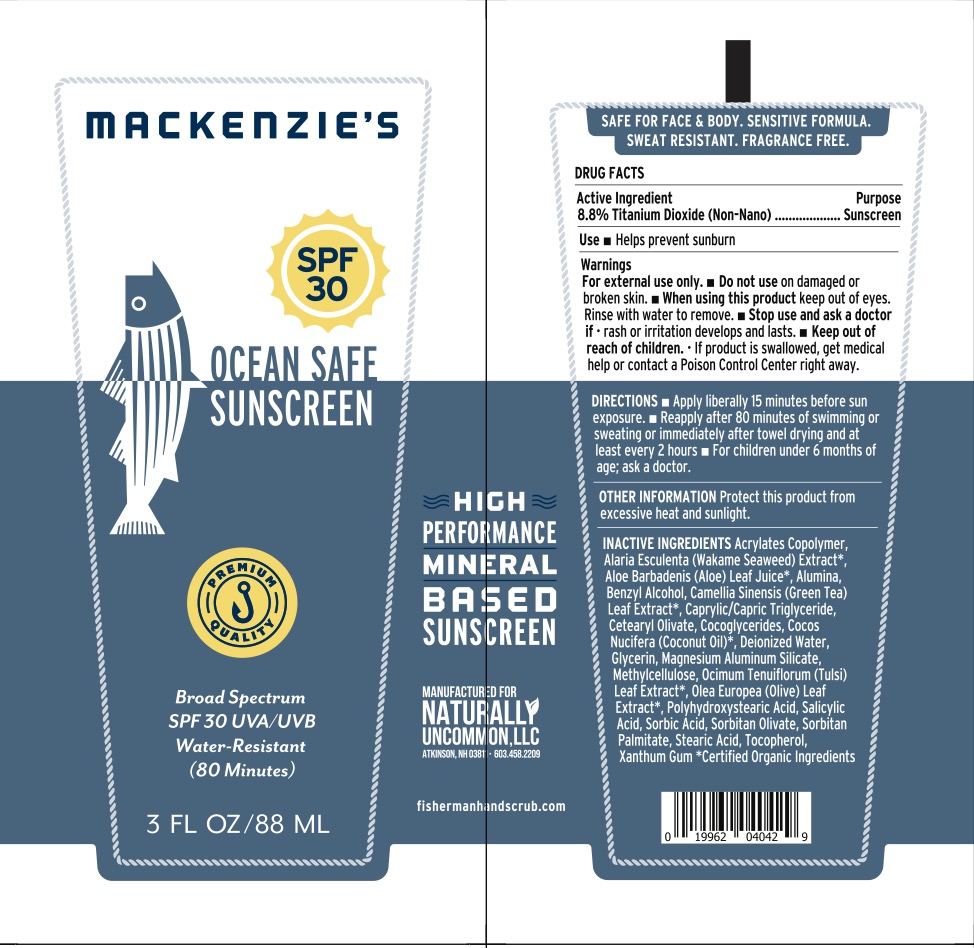 DRUG LABEL: MACKENZIES OCEAN SAFE SUNSCREEN
NDC: 80325-030 | Form: CREAM
Manufacturer: Naturally Uncommon, LLC
Category: otc | Type: HUMAN OTC DRUG LABEL
Date: 20240816

ACTIVE INGREDIENTS: TITANIUM DIOXIDE 8.8 g/100 mL
INACTIVE INGREDIENTS: WATER; GREEN TEA LEAF; HOLY BASIL LEAF; ALARIA ESCULENTA; OLEA EUROPAEA LEAF; ALOE; TRICAPRIN; COCO-GLYCERIDES; GLYCERIN; CETOSTEARYL ALCOHOL; CETYL PALMITATE; POLYHYDROXYSTEARIC ACID STEARATE; SORBITAN OLIVATE; CETEARYL OLIVATE; METHYLCELLULOSE, UNSPECIFIED; COCONUT OIL; STEARIC ACID; LUVISET 360; MAGNESIUM ALUMINUM SILICATE; SORBITAN MONOPALMITATE; TOCOPHEROL; XANTHAN GUM; ALUMINUM OXIDE; BENZYL ALCOHOL; SALICYLIC ACID; SORBIC ACID

Mackenzies SPF 30 Sunscreen

DRUG FACTS Active Ingredients

Titanium Dioxide (non-nano) 8.8%

Purpose

Sunscreen

Uses

■ Helps prevent sunburn.

Warnings

■ For external use only.
■ Do not use on damaged or broken skin.
■ Stop use and ask a doctor if rash occurs.
■ When using this product, keep out of eyes. Rinse with water to remove.

KEEP OUT OF REACH OF CHILDREN

If product is swallowed, get medical help or contact a Poison Control Center right away.

DIRECTIONS

■ Apply liberally 15 minutes before sun exposure.
■ Reapply after 80 minutes of swimming or sweating or immediately after towel drying and at least every 2 hours.
■ For children under 6 months of age; ask a doctor.

OTHER INFO

Protect this product from excessive heat and sunlight.

INACTIVE INGREDIENTS

Acrylates Copolymer, Alaria Esculenta (Wakame Seaweed) Extract*, Aloe Barbadensis (Aloe) Leaf Juice*, Alumina, Benzyl Alcohol, Camellia Sinensis (Green Tea) Leaf Extract*, Caprylic/Capric Triglyceride, Cetearyl Olivate, Cocoglycerides, Cocos Nucifera (Coconut Oil)*, Deionized Water, glycerin, Magnesium Aluminum Silicate, Methylcellulose, Ocimum Tenuiflorum (Tulsi) Leaf Extract*, Olea Europea (Olive) Leaf Extract*, Polyhydroxystearic Acid, Salicylic Acid, Sorbic Acid, Sorbitan Olivate, Sorbitan Palmitate, Stearic Acid, Tocopherol, Xanthan Gum.

*Certified Organic Ingredients